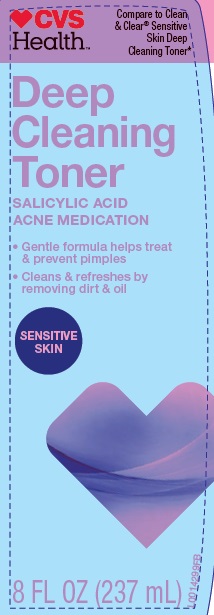 DRUG LABEL: Salicylic Acid
NDC: 59779-961 | Form: LIQUID
Manufacturer: CVS Pharmacy, Inc
Category: otc | Type: HUMAN OTC DRUG LABEL
Date: 20160215

ACTIVE INGREDIENTS: SALICYLIC ACID 5 mg/1 mL
INACTIVE INGREDIENTS: ALCOHOL; LAMINARIA DIGITATA; ALOE; BENZOPHENONE; DENATONIUM BENZOATE; DIMETHICONE; GLYCERIN; ISOCETETH-20; POLYETHYLENE GLYCOL 1500; SODIUM CITRATE; water; FD&C BLUE NO. 1

Drug facts

Active ingredient

Salicylic acid 0.5%

Purpose

Acne medication

Use

for the treatment of acne

Warnings

For external use only

Flammable. Keep away rom fire or flame.

When using this product

- skin irritation and dryness is more likely to occur if you use another topical acne medication at the same time. If irritation occurs, only use one topical acne medication at a time

Keep out of reach of children.

If swallowed, get medical help or contact a Poison Control Center right away

Directions

- clean the skin thoroughly before applying this product
- cover the entire affected area with a thin layer and rinse thoroughly one to three times daily
- because excessive drying of the skin may occur, start with one application daily, then gradually increase to two or three times daily if needed or as directed by a doctor
- if bothersome dryness or peeling occurs, reduce daily application to once a day or every other day

Inactive ingredients

alcohol (24.5%), algae extract, aloe barbadesis leaft extract, benzophenone-4, denatonium benzoate, dimethicone propyl PG-betaine, fragrance, glycerin, isoceteth-20, PEG-32, propylene glycol, sodium citrate, water, blue 1

*This product is not manufactured or distributed by Johnson & Johnson Consumer Products Company, distributor of Clean & Clear Sensitive Skin Deep Cleaning Astringent.

Distributed by: CVS Pharmacy, Inc.

One CVS Drive, Woonsocket, RI 02895

(c) 2015 CVS/pharmacy

CVS.com 1-800-SHOP CVS

Made in the USA with US and foreign components

DSP-TN-15000 DSP-MO-34 SDS-TN-15012

Principal Display Panel

Compare to Clean & Clear Sensitive Skin Deep Cleaning Toner*

CVS Health

Deep Cleaning Toner

salicylic acid acne medication

- gentle formula that treats and prevent pimples
- cleans & refreshes by removing dirt & oil

Sensitive skin

8 FL OZ (237 mL)